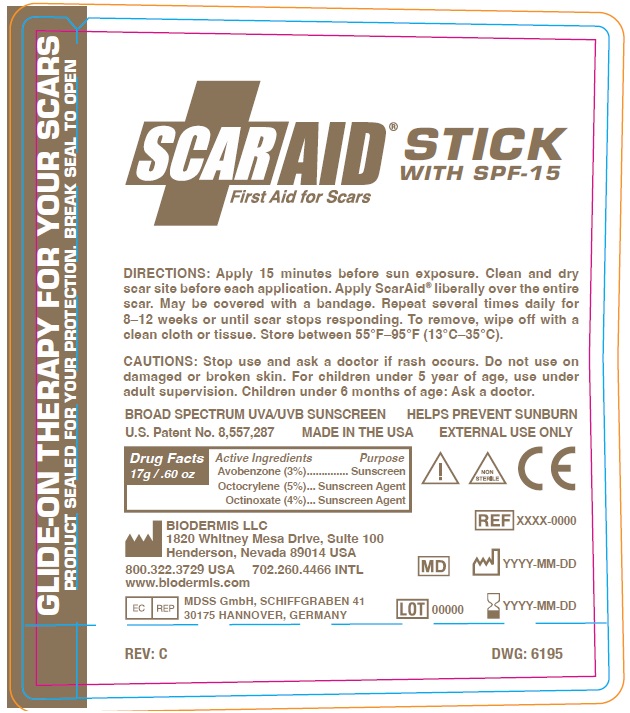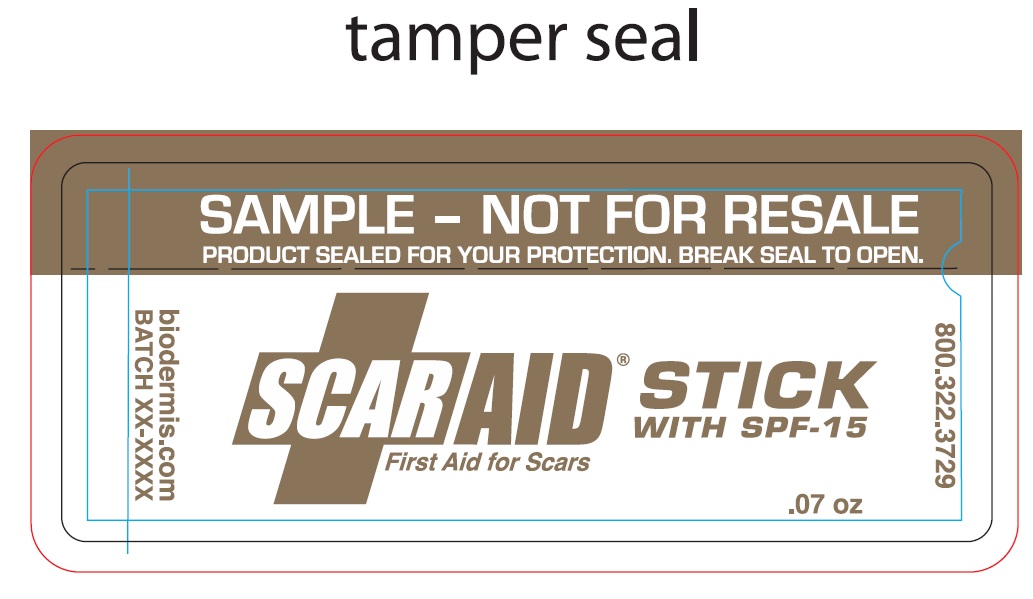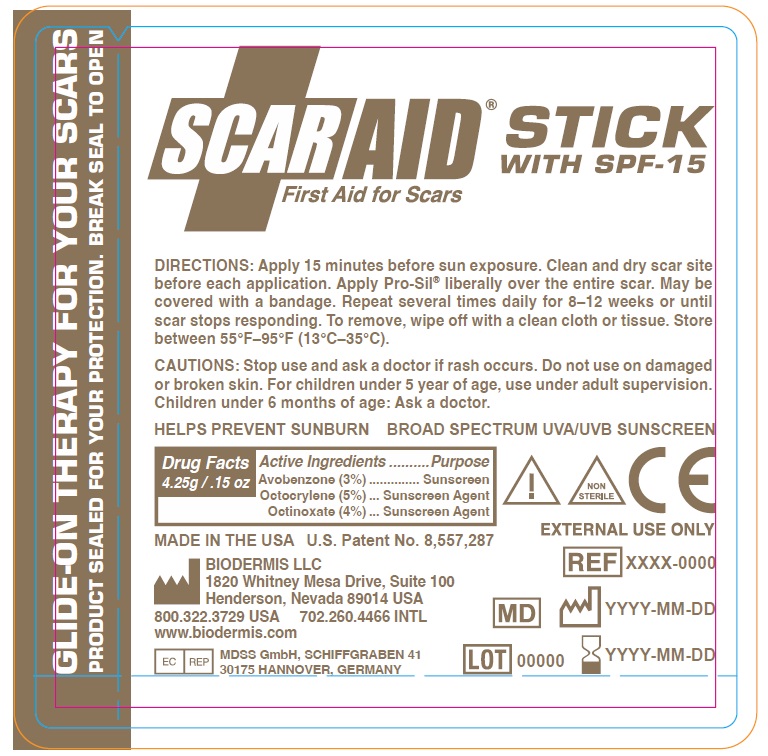 DRUG LABEL: ScarAid SPF
NDC: 84440-619 | Form: STICK
Manufacturer: Biodermis, LLC
Category: otc | Type: HUMAN OTC DRUG LABEL
Date: 20250811

ACTIVE INGREDIENTS: OCTINOXATE 40 mg/1 g; AVOBENZONE 30 mg/1 g; OCTOCRYLENE 50 mg/1 g
INACTIVE INGREDIENTS: SILICON 880 mg/1 g

ScarAid SPF

DESCRIPTION:

PROSIL SPF15

SILICONE STICK FOR SCARS

GLYDE-ON THERAPY FOR YOUR SCARS

ACTIVE INGREDIENTS:

Avobenzone - 3% Sunscreen

Octocrylene - 5% Sunscreen agent

Octinoxate - 4% Sunscreen agent

DOSAGE & ADMINISTRATION:

Apply 15 minutes before sun exposure. Clean and dry scar site before each application. Apply ScarAid® liberally over the entire
scar. May be covered with a bandage. Repeat several times daily for 8–12 weeks or until scar stops responding. To remove, wipe off with a clean cloth or tissue.

PURPOSE:

SILICONE STICK FOR SCARS

BROAD SPECTRUM UVA/UVB SUNSCREEN

HELPS PREVENT SUNBURN

INDICATIONS & USAGE:

SILICONE STICK FOR SCARS

BROAD SPECTRUM UVA/UVB SUNSCREEN

HELPS PREVENT SUNBURN

DIRECTIONS:

Apply 15 minutes before sun exposure. Clean and dry scar site
before each application. Apply ScarAid® liberally over the entire scar. May be
covered with a bandage. Repeat several times daily for 8–12 weeks or until
scar stops responding. To remove, wipe off with a clean cloth or tissue. Store
between 55°F–95°F (13°C–35°C).

WARNINGS:

FOR EXTERNAL USE ONLY

WARNINGS AND PRECAUTIONS:

EXTERNAL USE ONLY

CAUTIONS: Stop use and ask a doctor if rash occurs. Do not use on
damaged or broken skin. For children under 5 year of age, use under
adult supervision. Children under 6 months of age: Ask a doctor.

CAUTIONS:

Stop use and ask a doctor if rash occurs. Do not use on damaged
or broken skin. For children under 5 year of age, use under adult supervision.
Children under 6 months of age: Ask a doctor.

KEEP OUT OF REACH OF CHILDREN:

Ask a doctor about using SCARAID SPF with children under 6 months old.

STORAGE:

Store between 55°F–95°F (13°C–35°C).

CONTACT INFORMATION:

MADE IN THE USA U.S. Patent No. 8,557,287

BIODERMIS LLC

www.biodermis.com
1820 Whitney Mesa Drive, Suite 100

Henderson, Nevada 89014 USA

800.322.3729 (USA)

702.260.4466 (INTL)

EC REP: MDSS GmbH, SCHIFFGRABEN 41 30175 HANNOVER, GERMANY

INACTIVE INGREDIENTS:

Silicone

Primary Package Label

4.25g Tube:

17g Tube:

1g Sample Tube: